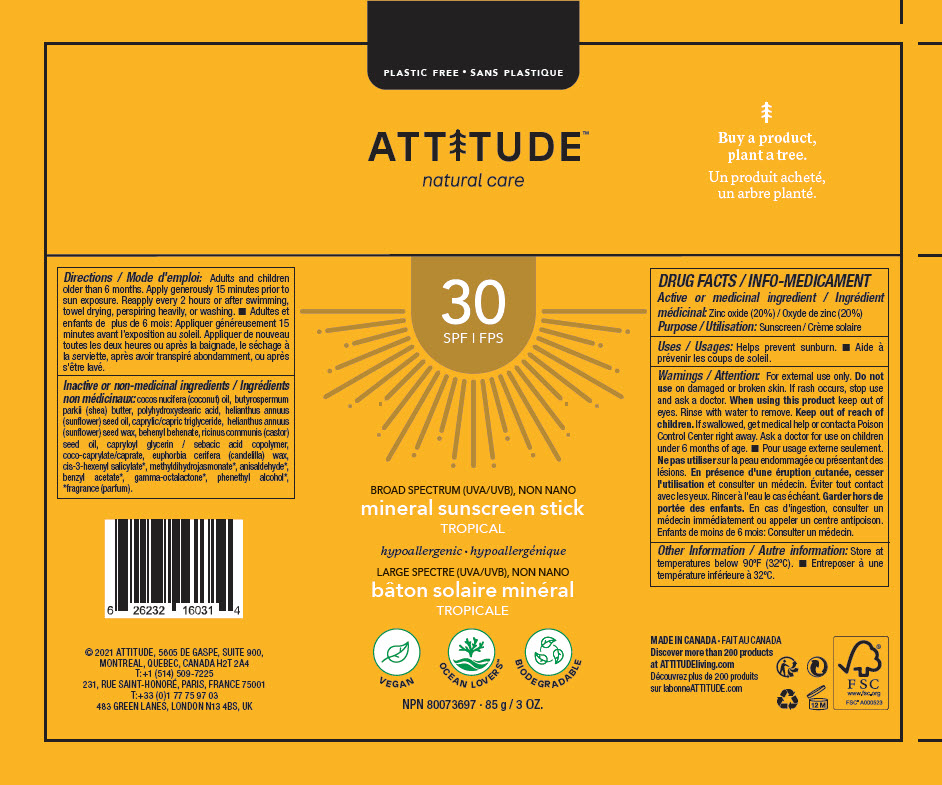 DRUG LABEL: Attitude mineral sunscreen tropical SPF 30
NDC: 61649-031 | Form: STICK
Manufacturer: Attitude DBA 9055-7588 Québec Inc.
Category: otc | Type: HUMAN OTC DRUG LABEL
Date: 20240328

ACTIVE INGREDIENTS: ZINC OXIDE 20 g/100 g
INACTIVE INGREDIENTS: COCONUT OIL; SHEA BUTTER; POLYHYDROXYSTEARIC ACID (2300 MW); SUNFLOWER OIL; MEDIUM-CHAIN TRIGLYCERIDES; HELIANTHUS ANNUUS SEED WAX; BEHENYL BEHENATE; CASTOR OIL; CAPRYLOYL GLYCERIN/SEBACIC ACID COPOLYMER (2000 MPA.S); COCOYL CAPRYLOCAPRATE; CANDELILLA WAX; 3-HEXENYL SALICYLATE, CIS-; METHYL DIHYDROJASMONATE (SYNTHETIC); P-ANISALDEHYDE; BENZYL ACETATE; PHENYLETHYL ALCOHOL; .GAMMA.-OCTALACTONE

Attitude mineral sunscreen stick tropical SPF 30

DRUG FACTS

Active or medicinal ingredient

Zinc oxide (20%)

Purpose

Sunscreen

Uses

Helps prevent sunburn.

Warnings

For external use only.

DO NOT USE

Do not useon damaged or broken skin. If rash occurs, stop use and ask a doctor.

WHEN USING

When using this productkeep out of eyes. Rinse with water to remove.

Keep out of reach of children.If swallowed, get medical help or contact a Poison Control Center right away. Ask a doctor for use on children under 6 months of age.

Other Information

Store at temperatures below 90°F (32°C).

Directions

Adults and children older than 6 months. Apply generously 15 minutes prior to sun exposure. Reapply every 2 hours or after swimming, towel drying, perspiring heavily, or washing.

Inactive or non-medicinal ingredients

cocos nucifera (coconut) oil, butyrospermum parkii (shea) butter, polyhydroxystearic acid, helianthus annuus (sunflower) seed oil, caprylic/capric triglyceride, helianthus annuus (sunflower) seed wax, behenyl behenate, ricinus communis (castor) seed oil, capryloyl glycerin / sebacic acid copolymer, coco-caprylate/caprate, euphorbia cerifera (candelilla) wax, cis-3-hexenyl salicylate*, methyldihydrojasmonate*, anisaldehyde*, benzyl acetate*, gamma-octalactone*, phenethyl alcohol*, *fragrance (parfum).

PRINCIPAL DISPLAY PANEL - 85 g Tube Label

PLASTIC FREE

ATTITUDE™

natural care

30
SPF

BROAD SPECTRUM (UVA/UVB), NON NANO

mineral sunscreen stick
TROPICAL

hypoallergenic

VEGAN
OCEAN LOVERS™
BIODEGRADABLE

NPN 80073697 ∙ 85 g / 3 OZ.